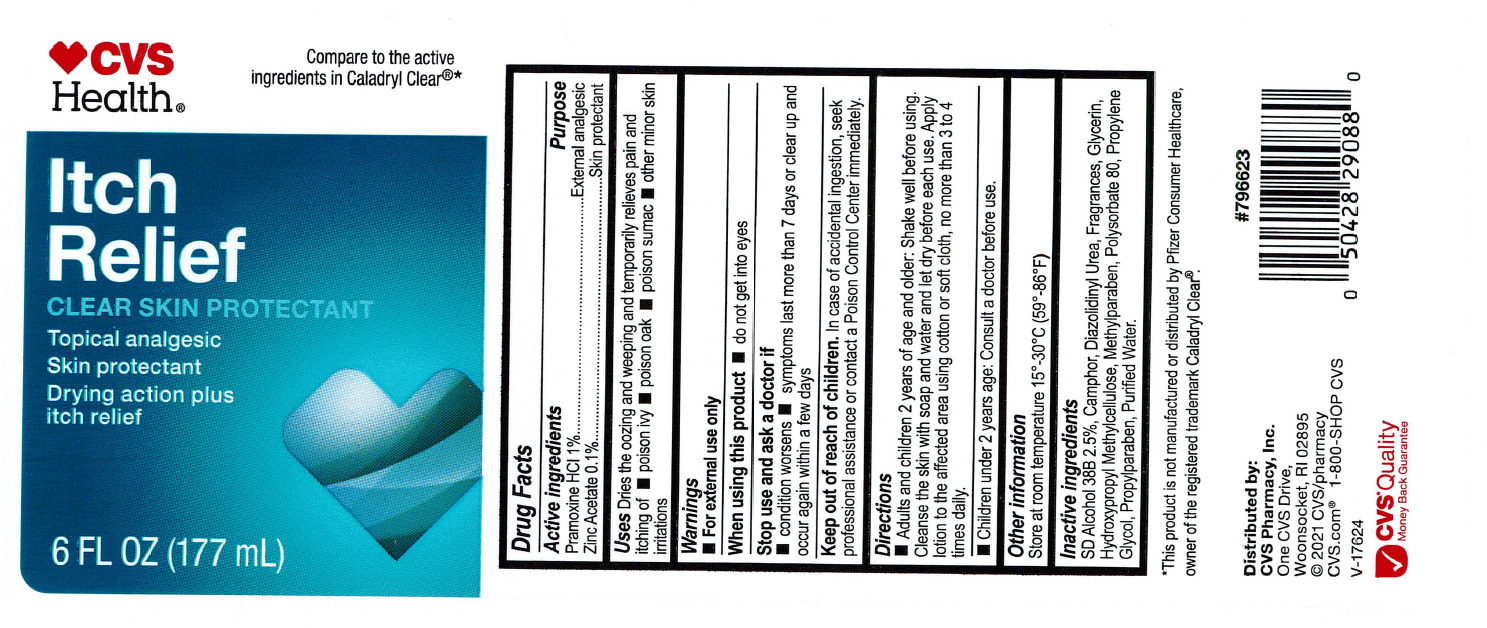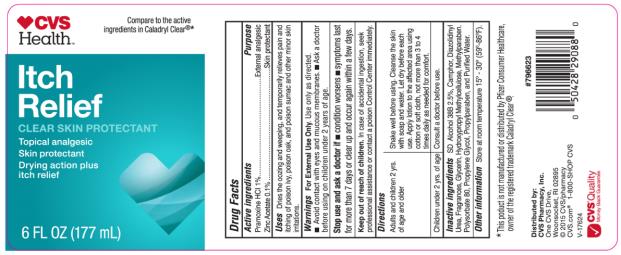 DRUG LABEL: CVS Itch Relief
NDC: 69842-400 | Form: LOTION
Manufacturer: CVS Pharmacy
Category: otc | Type: HUMAN OTC DRUG LABEL
Date: 20231220

ACTIVE INGREDIENTS: PRAMOXINE HYDROCHLORIDE 10 mg/1 mL; ZINC ACETATE 1 mg/1 mL
INACTIVE INGREDIENTS: ALCOHOL; CAMPHOR (NATURAL); DIAZOLIDINYL UREA; GLYCERIN; HYPROMELLOSE, UNSPECIFIED; METHYLPARABEN; POLYSORBATE 80; PROPYLENE GLYCOL; PROPYLPARABEN; WATER

CVS Itch Relief

CVS Itch Relief

Drug Facts

Active Ingredient

Pramoxine HCl 1%

Zinc Acetate 0.1%

Purpose

External Analgesic

Skin Protectant

Use

Dries the oozing and weeping, and temporarily relieves pain and itching of poison ivy, oak, and poison sumac and other minor skin irritations.

Warnings

For external use only. Use only as directed. Avoid contact with eyes and mucous membranes, Ask doctor before using in children under 2 years of age.

Stop use and ask a doctor if

condition worsens. Symptoms last for more than 7 days or clear up and occur again within a few days.

Keep out of reach of children.

In case of accidental ingestion, seek professional assistance or contact a Poison Control Center immediately.

Directions

- Adults and children 2 yrs. of age and older. Shake well before using. Cleanse the skin with soap and water and let dry. Apply to the affected area using cotton or soft cloth not more than 3 to 4 times daily as needed for comfort.
- Children under 2 yrs. of age: Consult a doctor before use.

Inactive Ingredient

- SD Alcohol 38B 2.5%, Camphor, Diazolidinyl Urea, Fragrances, Glycerin, Hydroxypropyl Methylcellulose, Methylparaben, Polysorbate 80, Propylene Glycol, Propylparaben, and Purified Water.

Other Information

- store at room temperature 15o – 30oC (59o – 85oF)

PRINCIPAL DISPLAY PANEL

CVS Health
Itch Relief
CLEAR SKIN PROTECTANT
6 FL OZ (177 mL)